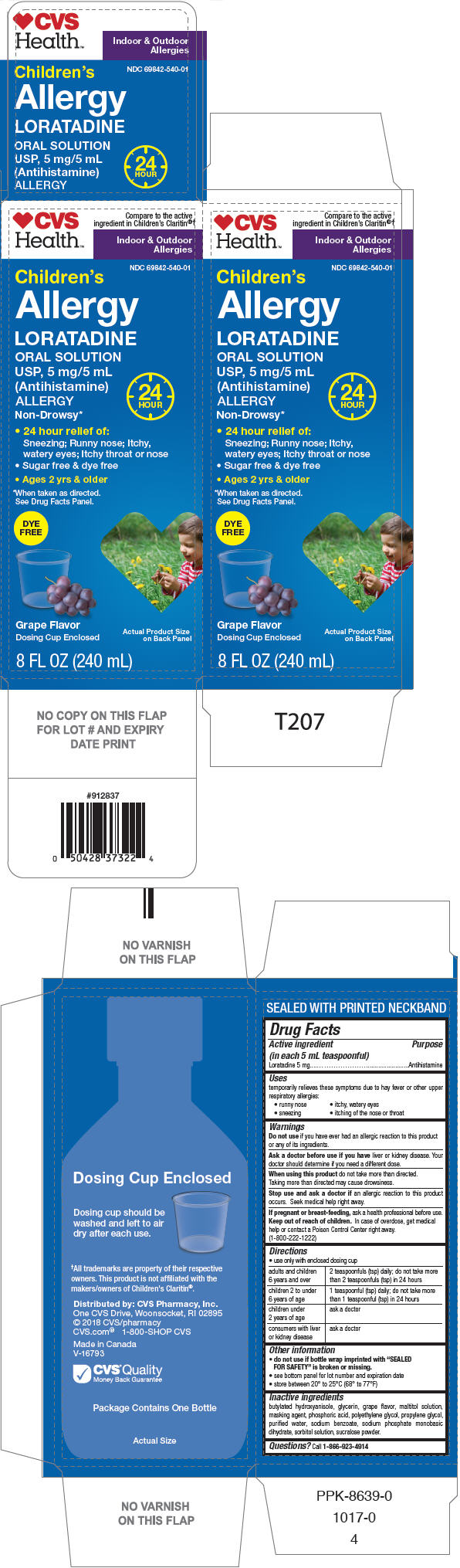 DRUG LABEL: Childrens Loratadine
NDC: 69842-540 | Form: SOLUTION
Manufacturer: CVS Pharmacy
Category: otc | Type: HUMAN OTC DRUG LABEL
Date: 20171130

ACTIVE INGREDIENTS: Loratadine 5 mg/5 mL
INACTIVE INGREDIENTS: butylated hydroxyanisole; glycerin; SORBITOL; POLYETHYLENE GLYCOL, UNSPECIFIED; phosphoric acid; propylene glycol; water; sodium benzoate; SODIUM PHOSPHATE, MONOBASIC, DIHYDRATE

Children's Loratadine Oral Solution
Sugar Free

Drug Facts

Active ingredient (in each 5 mL teaspoonful)

Loratadine 5 mg

Purpose

Antihistamine

Uses

temporarily relieves these symptoms due to hay fever or other upper respiratory allergies:

- runny nose
- itchy, watery eyes
- sneezing
- itching of the nose or throat

Warnings

Do not use if you have ever had an allergic reaction to this product or any of its ingredients.

Ask a doctor before use if you have liver or kidney disease. Your doctor should determine if you need a different dose.

When using this product do not take more than directed.

Taking more than directed may cause drowsiness.

Stop use and ask a doctor if an allergic reaction to this product occurs. Seek medical help right away.

PREGNANCY OR BREAST FEEDING

If pregnant or breast-feeding, ask a health professional before use.

Keep out of reach of children. In case of overdose, get medical help or contact a Poison Control Center right away. (1-800-222-1222)

Directions

- use only with enclosed dosing cup

adults and children 6 years and over | 2 teaspoonfuls (tsp) daily; do not take more than 2 teaspoonfuls (tsp) in 24 hours
children 2 to under 6 years of age | 1 teaspoonful (tsp) daily; do not take more than 1 teaspoonful (tsp) in 24 hours
children under 2 years of age | ask a doctor
consumers with liver or kidney disease | ask a doctor

Other information

- do not use if bottle wrap imprinted with "SEALED FOR SAFETY" is broken or missing.
- see bottom panel for lot number and expiration date
- store between 20° to 25°C (68° to 77°F)

Inactive ingredients

butylated hydroxyanisole, glycerin, grape flavor, maltitol solution, masking agent, phosphoric acid, polyethylene glycol, propylene glycol, purified water, sodium benzoate, sodium phosphate monobasic dihydrate, sorbitol solution, sucralose powder.

Questions?

Call 1-866-923-4914

Distributed by: CVS Pharmacy, Inc.
One CVS Drive, Woonsocket, RI 02895

PRINCIPAL DISPLAY PANEL - 240 mL Bottle Carton

CVS
Health™

Compare to the active
ingredient in Children's Claritin®†

Indoor & Outdoor
Allergies

NDC 69842-540-01

Children's
Allergy

LORATADINE
ORAL SOLUTION
USP, 5 mg/5 mL
(Antihistamine)
ALLERGY
Non-Drowsy*
24
HOUR

- 24 hour relief of:
  Sneezing; Runny nose; Itchy,
  watery eyes; Itchy throat or nose
- Sugar free & dye free
- Ages 2 yrs & older

*When taken as directed.
See Drug Facts Panel.

DYE
FREE

Grape Flavor
Dosing Cup Enclosed

Actual Product Size
on Back Panel

8 FL OZ (240 mL)